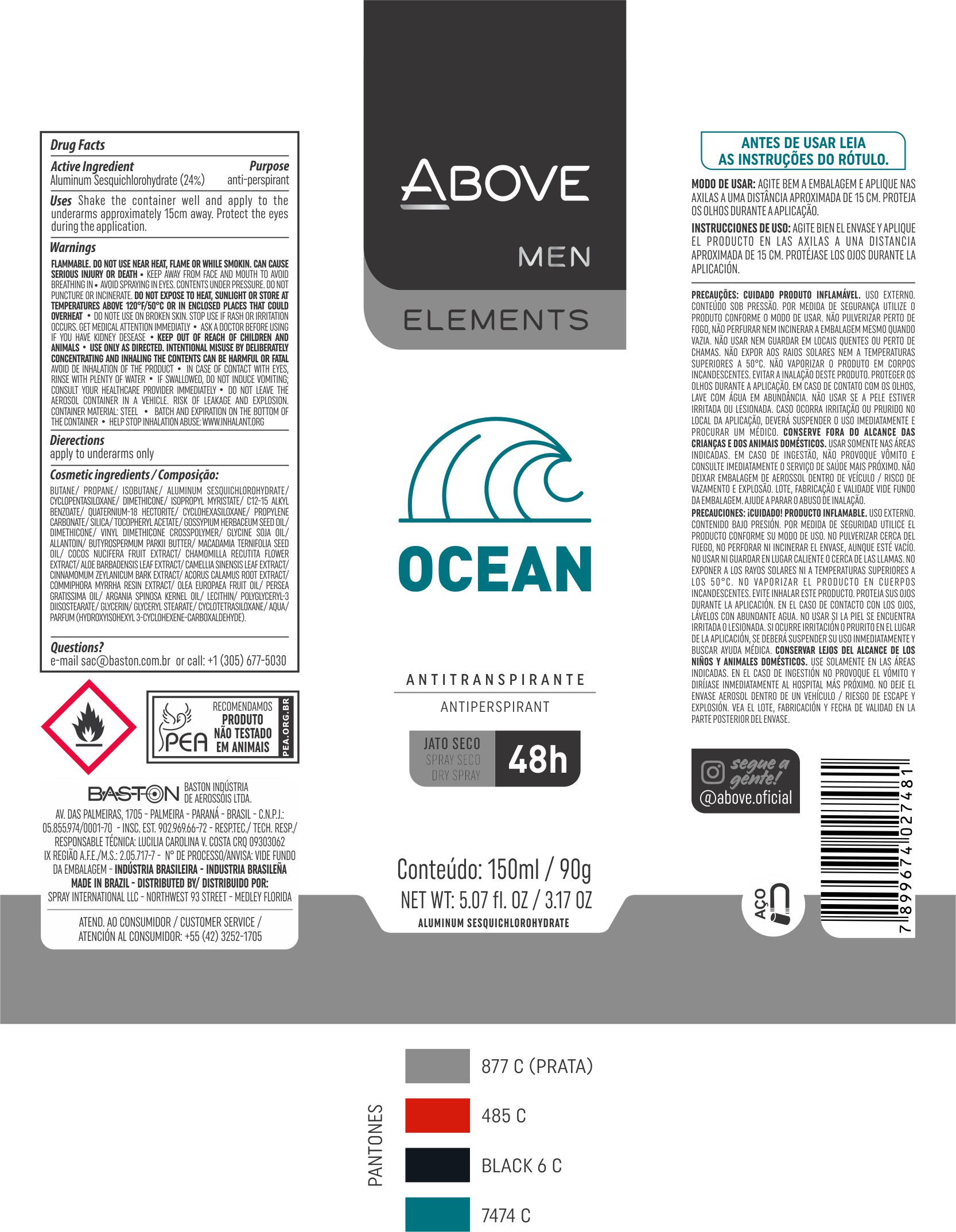 DRUG LABEL: Antiperspirant Above Elements Ocean
NDC: 73306-1117 | Form: AEROSOL, SPRAY
Manufacturer: Baston Indústria de Aerossóis Ltda
Category: otc | Type: HUMAN OTC DRUG LABEL
Date: 20241226

ACTIVE INGREDIENTS: ALUMINUM SESQUICHLOROHYDRATE 24 g/100 g
INACTIVE INGREDIENTS: LEVANT COTTON SEED; POLYGLYCERYL-3 DIISOSTEARATE; SILICA DIMETHYL SILYLATE; COCONUT; ARGAN OIL; GLYCERYL MONOSTEARATE; WATER; PROPANE; LECITHIN, SOYBEAN; .ALPHA.-TOCOPHEROL ACETATE; VINYL DIMETHICONE/METHICONE SILSESQUIOXANE CROSSPOLYMER; DISTEARDIMONIUM HECTORITE; CINNAMON BARK OIL; PROPYLENE CARBONATE; ALOE VERA LEAF; DIMETHICONE; GLYCERIN; ACORUS CALAMUS ROOT; ALLANTOIN; BUTANE; CHAMOMILE; ISOBUTANE; ISOPROPYL MYRISTATE; AVOCADO OIL; GREEN TEA LEAF; CYCLOMETHICONE 5; MACADAMIA OIL; SHEA BUTTER; MYRRH OIL

Antiperspirant Above Elements Ocean Aerosol